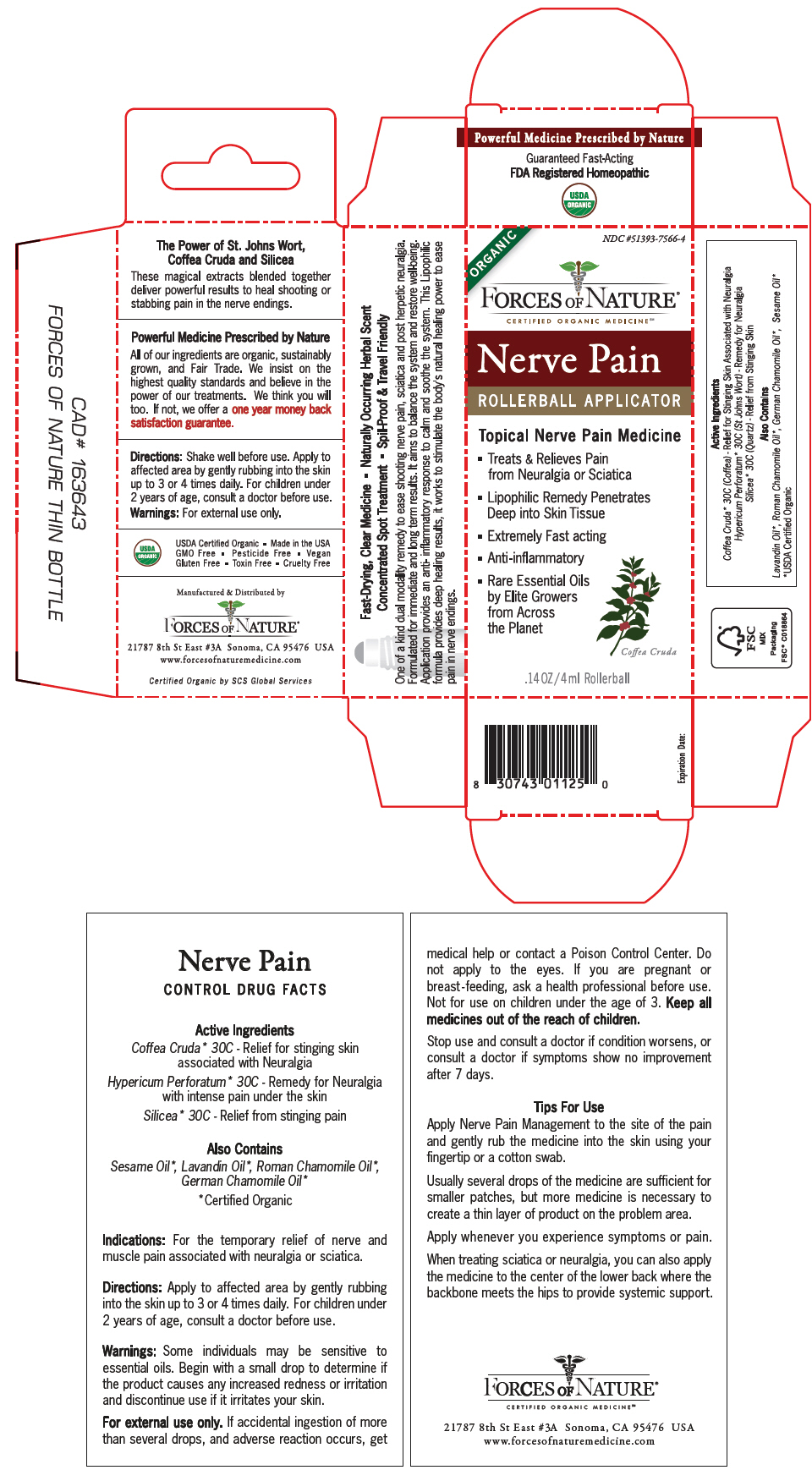 DRUG LABEL: Nerve Pain
NDC: 51393-7566 | Form: SOLUTION/ DROPS
Manufacturer: Forces of Nature
Category: homeopathic | Type: HUMAN OTC DRUG LABEL
Date: 20210709

ACTIVE INGREDIENTS: Arabica Coffee Bean 30 [hp_C]/100 mL; Silicon Dioxide 30 [hp_C]/100 mL; Hypericum Perforatum Whole 30 [hp_C]/100 mL
INACTIVE INGREDIENTS: Lavandula Dentata Whole; CHAMAEMELUM NOBILE WHOLE; Chamaemelum Nobile Flower; Sesame Oil

Nerve Pain Management

CONTROL DRUG FACTS

Active Ingredients

PURPOSE

Coffea Cruda [Certified Organic] 30C - Relief for stinging skin associated with Neuralgia

Hypericum Perforatum 30C - Remedy for Neuralgia with intense pain under the skin

Silicea 30C - Relief from stinging pain

Also Contains

Sesame Oil, Lavandin Oil, Roman Chamomile Oil, German Chamomile Oil

Indications

For the temporary relief of nerve and muscle pain associated with neuralgia or sciatica.

Directions

Apply to affected area by gently rubbing into the skin up to 3 or 4 times daily. For children under 2 years of age, consult a doctor before use.

Warnings

Some individuals may be sensitive to essential oils. Begin with a small drop to determine if the product causes any increased redness or irritation and discontinue use if it irritates your skin.

For external use only. If accidental ingestion of more than several drops, and adverse reaction occurs, get medical help or contact a Poison Control Center. Do not apply to the eyes. If you are pregnant or breast - feeding, ask a health professional before use. Not for use on children under the age of 3.

KEEP OUT OF REACH OF CHILDREN

Keep all medicines out of the reach of children.

Stop use and consult a doctor if condition worsens, or consult a doctor if symptoms show no improvement after 7 days.

Manufactured & Distributed by
FORCES OF NATURE®
21787 8th St East #3A Sonoma, CA 95476 USA

PRINCIPAL DISPLAY PANEL - 4 ml Bottle Box

ORGANIC

NDC #51393-7566-4

FORCES OF NATURE®
CERTIFIED ORGANIC MEDICINESM

Nerve Pain
ROLLERBALL APPLICATOR

Topical Nerve Pain Medicine

- Treats & Relieves Pain
  from Neuralgia or Sciatica
- Lipophilic Remedy Penetrates
  Deep into Skin Tissue
- Extremely Fast acting
- Anti-inflammatory
- Rare Essential Oils
  by Elite Growers
  from Across
  the Planet

Coffea Cruda

.14 OZ/4 ml Rollerball